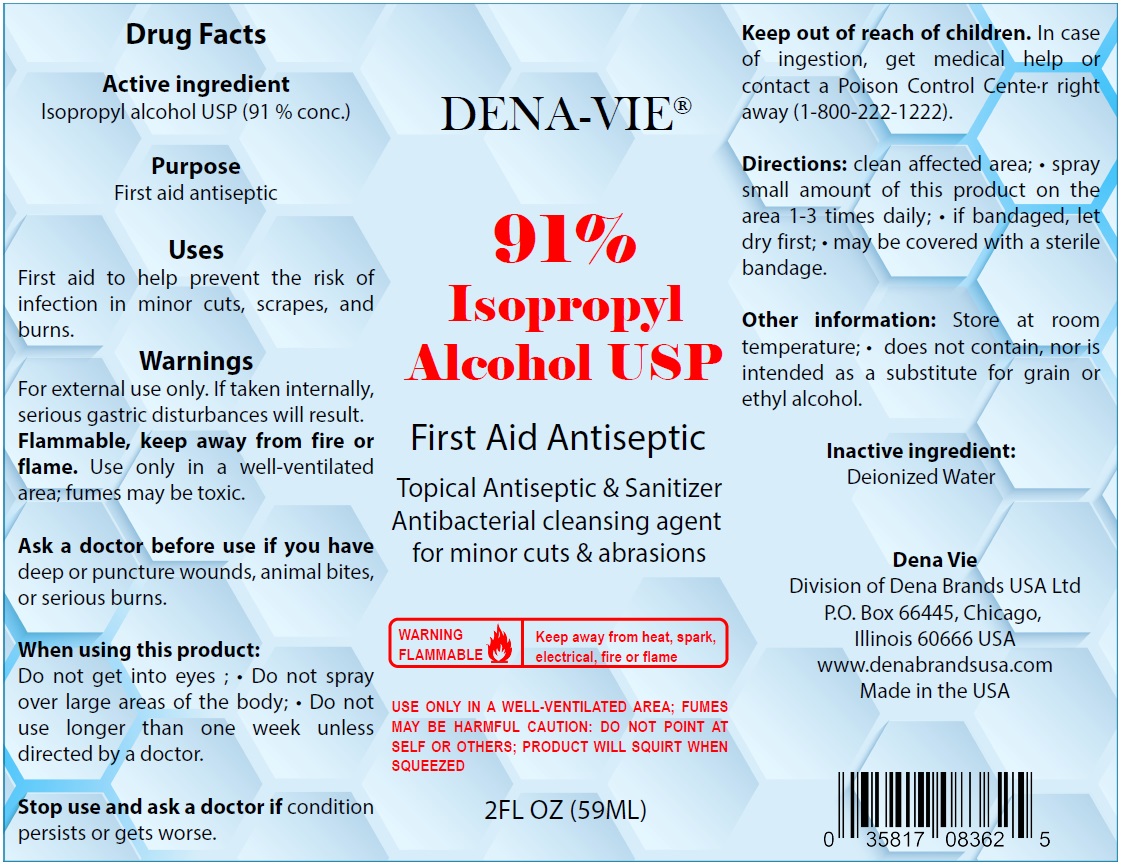 DRUG LABEL: Dena-Vie First Aid Antiseptic
NDC: 80937-083 | Form: SPRAY
Manufacturer: Dena Brands Usa Ltd.
Category: otc | Type: HUMAN OTC DRUG LABEL
Date: 20220128

ACTIVE INGREDIENTS: ISOPROPYL ALCOHOL 91 mL/100 mL
INACTIVE INGREDIENTS: WATER

DENA-VIE® First Aid Antiseptic

Active ingredient

Isopropyl alcohol USP (91 % conc.)

Purpose

First aid antiseptic

Uses

First aid to help prevent the risk of infection in minor cuts, scrapes, and burns.

Warnings

For external use only. If taken internally, serious gastric disturbances will result. Flammable, keep away from fire or flame. Use only in a well-ventilated area; fumes may be toxic.

Ask a doctor before use if you have deep or puncture wounds, animal bites, or serious burns.

When using this product:

Do not get into eyes ; • Do not spray over large areas of the body; • Do not use longer than one week unless directed by a doctor.

Stop use and ask a doctor if condition persists or gets worse.

Keep out of reach of children. In case of ingestion, get medical help or contact a Poison Control Center right away (1-800-222-1222).

Directions:

clean affected area; • spray small amount of this product on the area 1-3 times daily; • if bandaged, let dry first; • may be covered with a sterile bandage.

Other information:

Store at room temperature; • does not contain, nor is intended as a substitute for grain or ethyl alcohol.

Inactive ingredient:

Deionized Water

Topical Antiseptic & Sanitizer Antibacterial cleansing agent for minor cuts & abrasions

WARNING FLAMMABLE

Keep away from heat, spark, electrical, fire or flame.

USE ONLY IN A WELL-VENTILATED AREA; FUMES MAY BE HARMFUL CAUTION: DO NOT POINT AT SELF OR OTHERS; PRODUCT WILL SQUIRT WHEN SQUEEZED

Dena Vie

Division of Dena Brands USA Ltd

P.O. Box 66445, Chicago, Illinois 60666 USA

www.denabrandsusa.com

Made in the USA